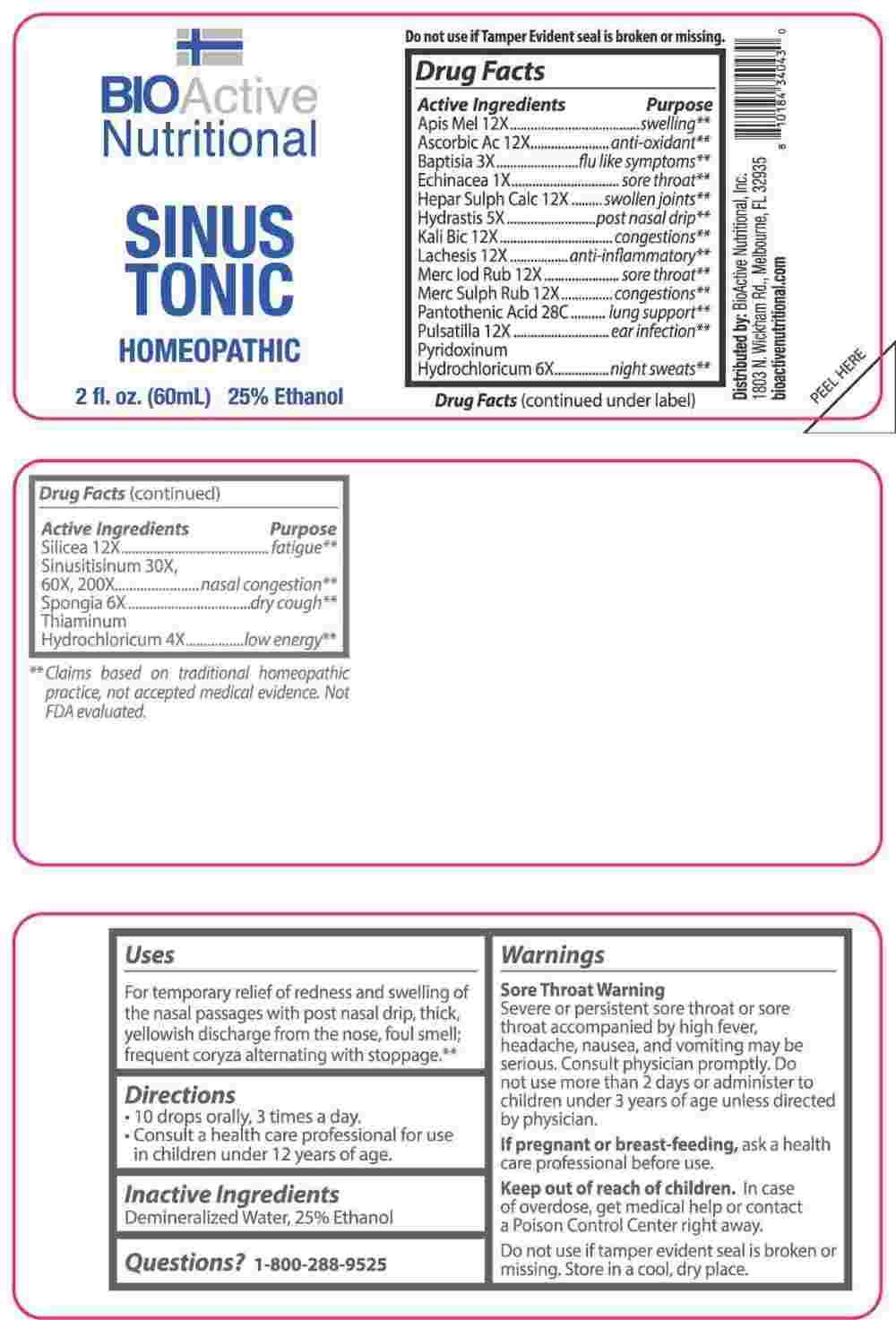 DRUG LABEL: Sinus Tonic
NDC: 43857-0532 | Form: LIQUID
Manufacturer: BioActive Nutritional, Inc.
Category: homeopathic | Type: HUMAN OTC DRUG LABEL
Date: 20250520

ACTIVE INGREDIENTS: ECHINACEA ANGUSTIFOLIA WHOLE 1 [hp_X]/1 mL; BAPTISIA TINCTORIA ROOT 3 [hp_X]/1 mL; THIAMINE HYDROCHLORIDE 4 [hp_X]/1 mL; GOLDENSEAL 5 [hp_X]/1 mL; PYRIDOXINE HYDROCHLORIDE 6 [hp_X]/1 mL; SPONGIA OFFICINALIS SKELETON, ROASTED 6 [hp_X]/1 mL; APIS MELLIFERA 12 [hp_X]/1 mL; ASCORBIC ACID 12 [hp_X]/1 mL; CALCIUM SULFIDE 12 [hp_X]/1 mL; POTASSIUM DICHROMATE 12 [hp_X]/1 mL; LACHESIS MUTA VENOM 12 [hp_X]/1 mL; MERCURIC IODIDE 12 [hp_X]/1 mL; MERCURIC SULFIDE 12 [hp_X]/1 mL; PULSATILLA PRATENSIS WHOLE 12 [hp_X]/1 mL; SILICON DIOXIDE 12 [hp_X]/1 mL; SINUSITISINUM 30 [hp_X]/1 mL; PANTOTHENIC ACID 28 [hp_C]/1 mL
INACTIVE INGREDIENTS: WATER; ALCOHOL

DRUG FACTS:

ACTIVE INGREDIENTS:

Apis Mellifica 12X, Ascorbic Acid 12X, Baptisia Tinctoria 3X, Echinacea 1X, Hepar Sulphuris Calcareum 12X, Hydrastis Canadensis 5X, Kali Bichromicum 12X, Lachesis Mutus 12X, Mercurius Iodatus Ruber 12X, Mercurius Sulphuratus Ruber 12X, Pantothenic Acid 28C, Pulsatilla 12X, Pyridoxinum Hydrochloricum 6X, Silicea 12X, Sinusitisinum 30X, 60X, 200X, Spongia Tosta 6X, Thiaminum, Hydrochloricum 4X.

PURPOSE:

Apis Mellifica - swelling,** Ascorbic Acid – anti-oxidant,** Baptisia Tinctoria – flu like symptoms,** Echinacea – sore throat,** Hepar Sulphuris Calcareum – swollen joints,** Hydrastis Canadensis – post nasal drip,** Kali Bichromicum - congestions,** Lachesis Mutus – anti-inflammatory,** Mercurius Iodatus Ruber – sore throat,** Mercurius Sulphuratus Ruber - congestions,** Pantothenic Acid – lung support,** Pulsatilla – ear infection,** Pyridoxinum Hydrochloricum – night sweats,** Silicea - fatigue,** Sinusitisinum – nasal congestion,** Spongia Tosta – dry cough,** Thiaminum, Hydrochloricum – low energy**

**Claims based on traditional homeopathic practice, not accepted medical evidence. Not FDA evaluated.

USES:

For temporary relief of redness and swelling of the nasal passages with post nasal drip, thick, yellowish discharge from the nose, foul smell; frequent coryza alternating with stoppage.**

**Claims based on traditional homeopathic practice, not accepted medical evidence. Not FDA evaluated.

WARNINGS:

Sore Throat Warning

Severe or persistent sore throat or sore throat accompanied by high fever, headache, nausea, and vomiting may be serious. Consult physician promptly. Do not use more than 2 days or administer to children under 3 years of age unless directed by physician.

If pregnant or breast-feeding, ask a health care professional before use.

Keep out of reach of children. In case of overdose, get medical help or contact a Poison Control Center right away.

Do not use if tamper evident seal is broken or missing.

Store in a cool, dry place.

KEEP OUT OF REACH OF CHILDREN:

In case of overdose, get medical help or contact a Poison Control Center right away.

DIRECTIONS:

• 10 drops orally, 3 times a day.

• Consult a health care professional for use in children under 12 years of age.

INACTIVE INGREDIENTS:

Demineralized Water, 25% Ethanol

QUESTIONS:

Distributed by:

BioActive Nutritional, Inc.

1803 N. Wickham Rd.

Melbourne, FL 32935

bioactivenutritional.com

1-800-288-9525

PACKAGE LABEL DISPLAY:

BIOActive Nutritional

SINUS TONIC

HOMEOPATHIC

2fl. oz. (60mL)